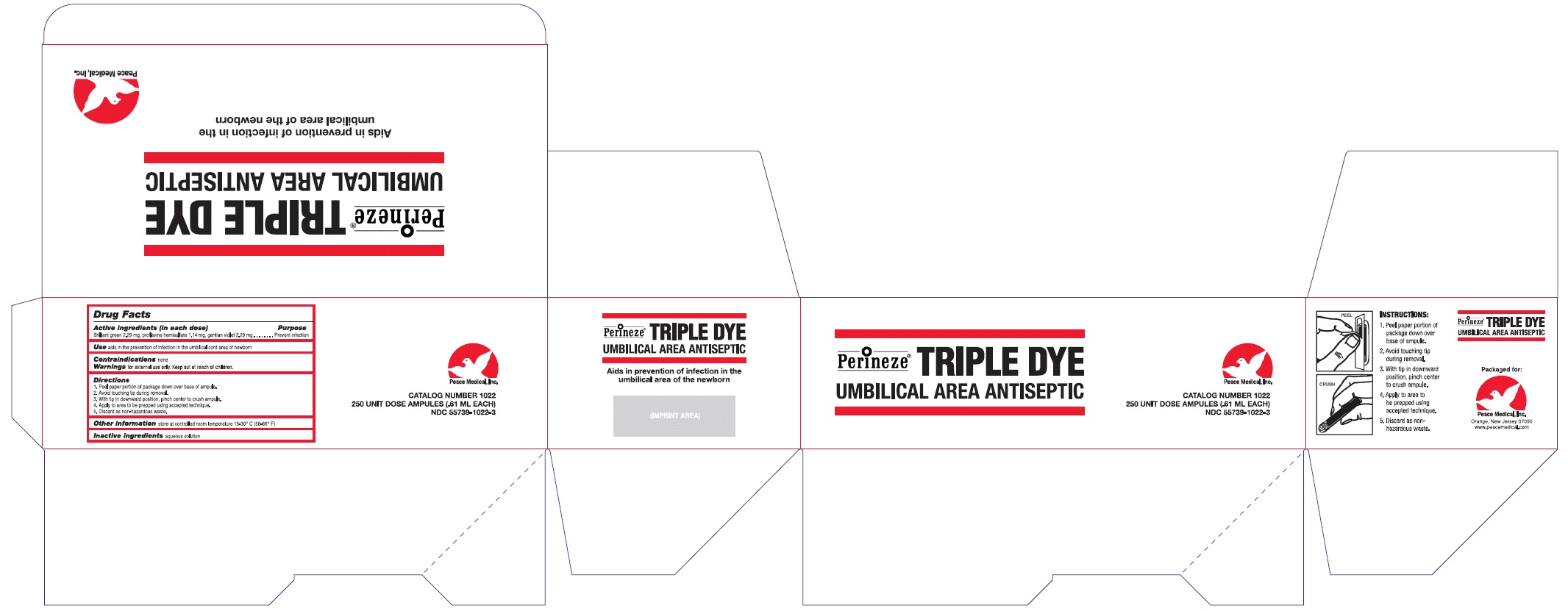 DRUG LABEL: Perineze Triple Dye
NDC: 55739-1022 | Form: SOLUTION
Manufacturer: Peace Medical Inc.
Category: otc | Type: HUMAN OTC DRUG LABEL
Date: 20110928

ACTIVE INGREDIENTS: BRILLIANT GREEN 2.29 mg/0.61 mL; PROFLAVINE HEMISULFATE 1.14 mg/0.61 mL; GENTIAN VIOLET 2.29 mg/0.61 mL
INACTIVE INGREDIENTS: WATER

Drug Facts

Active Ingredients (in each dose)

Brilliant green 2.29 mg

Proflavine hemisulfate 1.14 mg

gentian violet 2.29 mg

Purpose

Prevent Infection

Use

aids in the prevention of infection in the umbilical cord area of newborn

Contraindications

none

Warnings

for external use only

KEEP OUT OF REACH OF CHILDREN

Directions

- Peel paper portion of package down over base of ampule
- Avoid touching tip during removal
- With tip in downward position, pinch center to crush ampule.
- Apply to area to be prepped using accepted technique.
- Discard as non-hazardous waste.

Other information

store at controlled room temperature 15-30oC (58-86oF)

Inactive ingredients

aqueous solution

Perineze Triple Dye Package Label

Perineze® Triple Dye

UMBILICAL AREA ANTISEPTIC

Peace Medical, Inc.

CATALOG NUMBER 1022
250 UNIT DOSE AMPULES (.61 ML EACH)
NDC 55739-1022-3

Aids in prevention of infection in the umbilical area of the newborn.